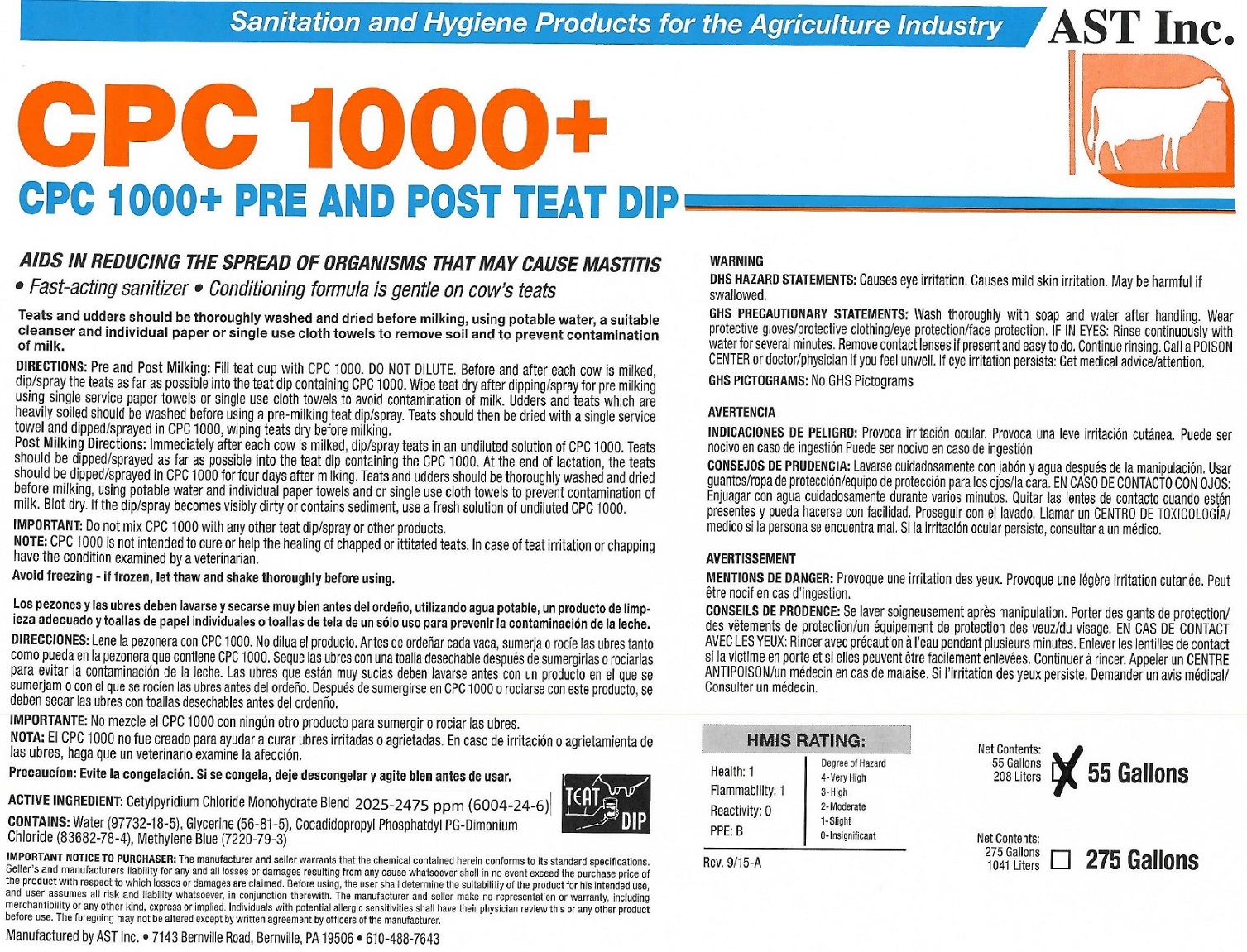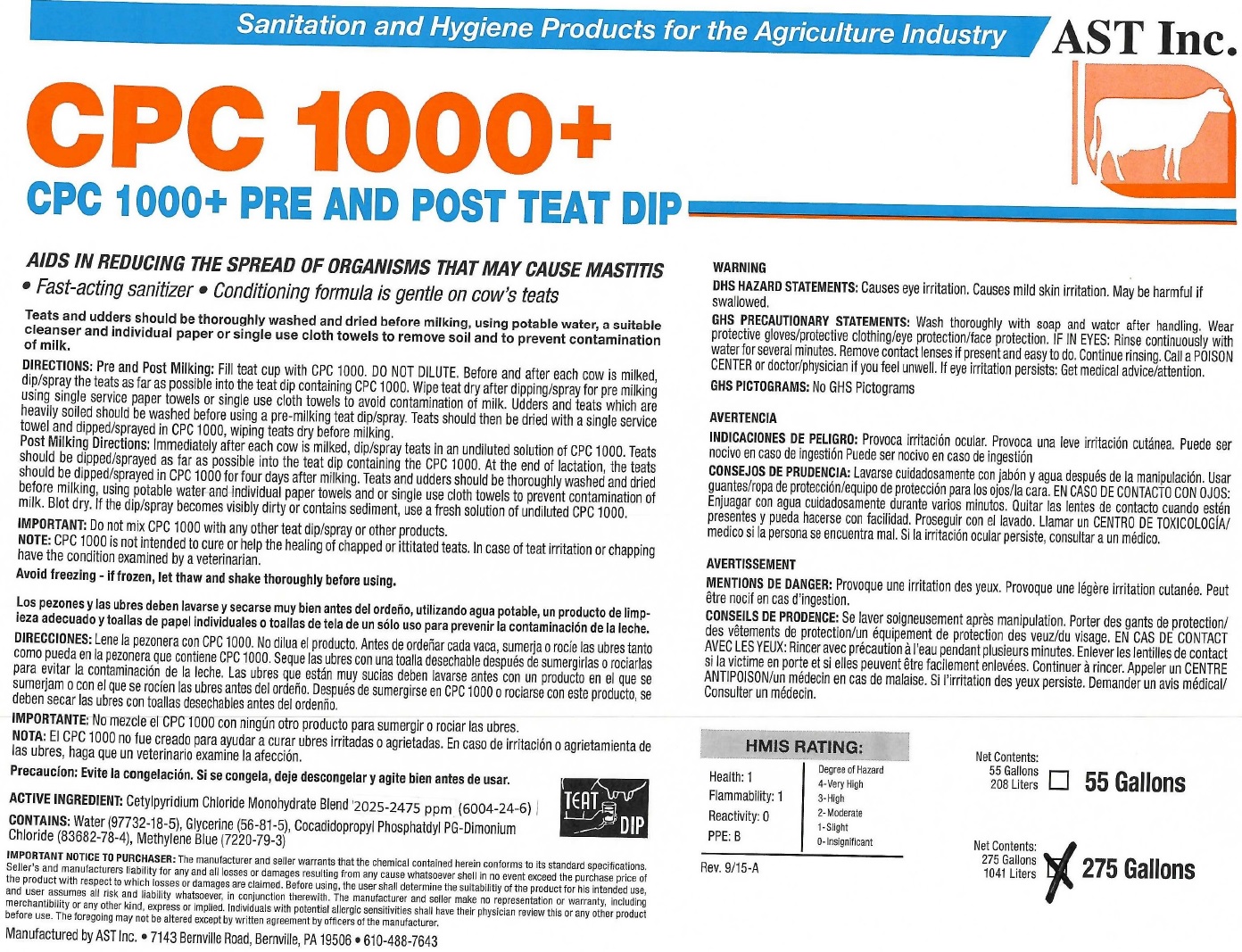 DRUG LABEL: CPC 1000 Pre and post teat dip
NDC: 52657-0106 | Form: LIQUID
Manufacturer: Advanced Skin Technologies Inc.
Category: animal | Type: OTC ANIMAL DRUG LABEL
Date: 20220827

ACTIVE INGREDIENTS: CETYLPYRIDINIUM CHLORIDE 0.00225 ug/1 L

CPC 1000 + Pre and post teat dip

AIDS IN REDUCING THE SPREAD OF ORGANISMS THAT MAY CAUSE MASTITIS

- Fast-acting sanitizer
- Conditioning formula is gentle on cow's teats

Treats and udders should be thoroughly washed and dired before milking, using potable water, a suitable cleanser and individual paper or single use cloth towels to remove soil and to prevent contamination of milk.

DIRECTIONS:

Pre and post Milking: Fill teat cup with CPC 1000. DO NOT DILUTE. Before and after each cow is milked, dip/spray the teats as far as possible into the teat dip containing CPC 1000. Wipe teat dry after dipping/spray for pre milking using single service paper towels or single use cloth towels to avoid contamination of milk. Udders and teats which are heavily soiled should be washed before using a pre-milking teat dip/spray. Teats should then be dried with a single serivice towel and dipped/sprayed in CPC 1000, wiping teats dry before milking.

Post Milking Directions: Immediately after each cow is milked, dip/spray teats in an undiluted solution of CPC 1000. Teats should be dipped/sprayed as fas as possible into the teat dip containing the CPC 1000. At the end of lactation, the teats should be dipped/sprayed in CPC 1000 for four days after milking. Teats and udders should be thoroughly washed and dired before milking, using potable water and individual paper towels and or single use cloth to prevent cotamination of milk. Blot dry. If the dip/spray becomes visibly dirty or contains sediment use a fresh solution of undilluted CPC 1000.

IMPORTANT:

Do not mix CPC 1000 with any other teat dip/spray or other products.

NOTE: CPC 1000 is not intened to cure or help the healing of chapped or ittitated teats. In case of teat irritation or chapping have the condition exmined by a veterinarian.

Avoid freezing - if frozen, let thaw and shake thoroughly before using.

ACTIVE INGREDIENT:

Cetylpyridinium Chloride Monohydrate Brand 2025-2475 ppm (6004-24-6)

CONTAINS: Water (97732-18-5), Glycerine (56-81-5), Cocadidopropyl Phosphatidyl PG-Dimonium Chloride (83682-78-4), Methylene Blue (7220-79-3)

HMIS RATING:

Health: 1 Degree of Hazard

Flammability:1 4-Very High

Reactivity:0 3-High

PPE: B 2-Moderate

1-Slight

0-insignificant